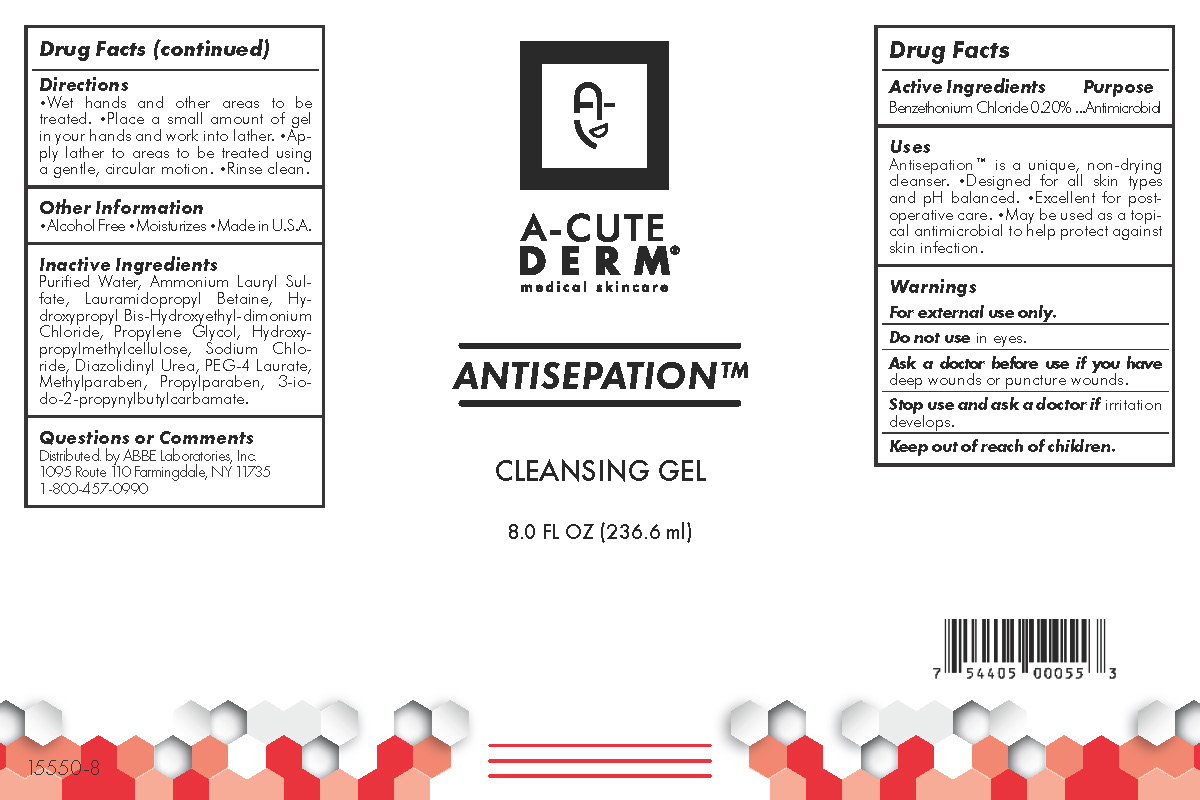 DRUG LABEL: A-Cute Derm Antisepation
NDC: 68605-7171 | Form: GEL
Manufacturer: ABBE Laboratories, Inc.
Category: otc | Type: HUMAN OTC DRUG LABEL
Date: 20260124

ACTIVE INGREDIENTS: BENZETHONIUM CHLORIDE 2 mg/1 mL
INACTIVE INGREDIENTS: AMMONIUM LAURYL SULFATE; HYDROXYPROPYL BIS-HYDROXYETHYLDIMONIUM CHLORIDE; HYPROMELLOSES; SODIUM CHLORIDE; DIAZOLIDINYL UREA; PEG-4 LAURATE; METHYLPARABEN; IODOPROPYNYL BUTYLCARBAMATE; LAURAMIDOPROPYL BETAINE; PROPYLPARABEN; PROPYLENE GLYCOL; WATER

DRUG FACTS

A-Cute Derm Antisepation Cleansing Gel

Active Ingredients

Benzethonium Chloride (0.2%)

Purpose

Antimicrobial

Uses

Antisepation™ is a unique, non-drying cleanser. •Designed for all skin types and pH balanced. •Excellent for postoperative care. •May be used as a topical antimicrobial to help protect against skin infection.

Warnings

For external use only.
Do not use in eyes.
Ask a doctor before use if you have deep wounds or puncture wounds.
Stop use and ask a doctor if irritation develops.

Directions

•Wet hands and other areas to be treated.

•Place a small amount of gel in your

hands and work into lather. •Apply lather

to areas to be treated using a gentle, circular

motion. •Rinse clean.

Other Information

•Alcohol Free •Moisturizes •Made in USA

Inactive ingredients

Purified Water, Ammonium Lauryl Sulfate,

Lauramidopropyl Betaine, Hydroxypropyl

Bis-Hydroxyethyl-dimonium Chloride,

Propylene Glycol, Hydroxypropylmethylcellulose,

Sodium Chloride, Diazolidinyl

Urea, PEG-4 Laurate, Methylparaben,

Propylparaben, 3-iodo-2-propynylbutylcarbamate.

Questions or Comments

Distributed by ABBE Laboratories, Inc.
1095 Route 110 Farmingdale, NY 11735
1-800-457-0990

Principal Display Panel

A-Cute

Derm®

medical skincare

Antisepation™

Cleansing Gel

8.0 FL OZ (236.6 ml)